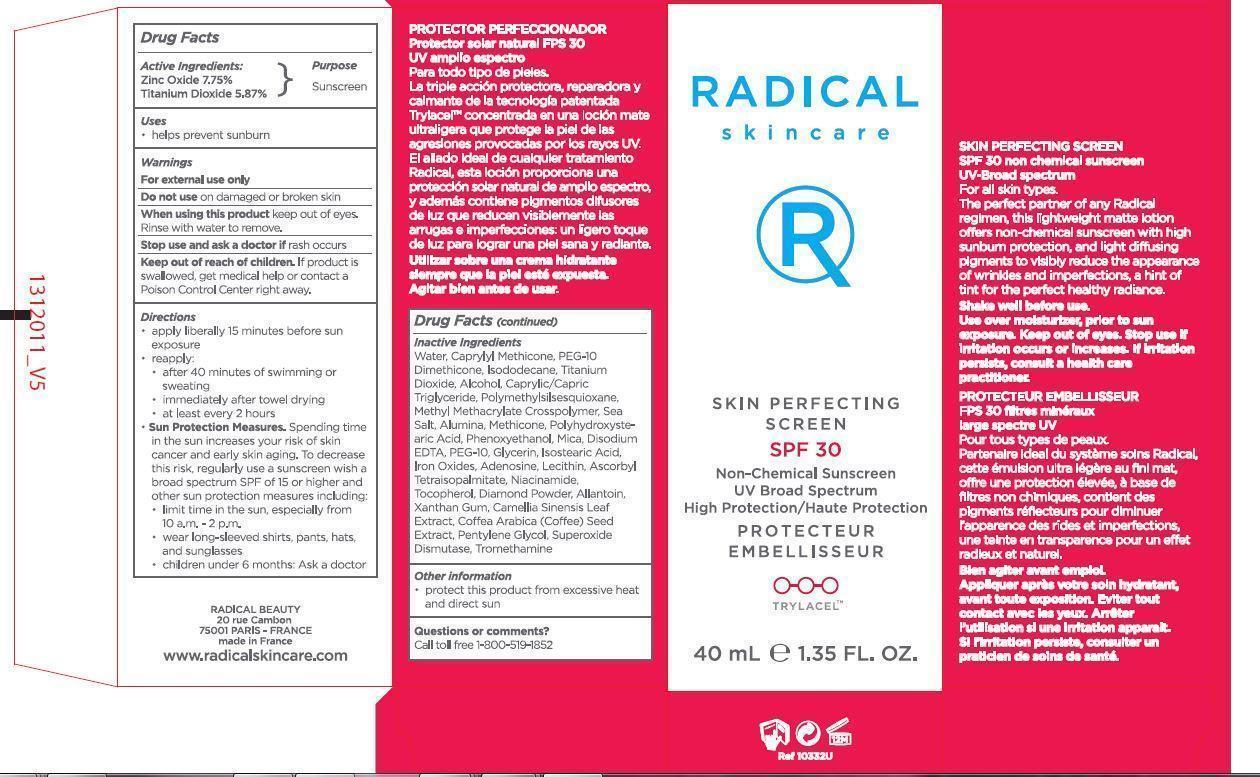 DRUG LABEL: RADICAL SKINCARE SKIN PERFECTING SCREEN SPF 30
NDC: 62510-001 | Form: LOTION
Manufacturer: RADICAL BEAUTY USA INC
Category: otc | Type: HUMAN OTC DRUG LABEL
Date: 20150331

ACTIVE INGREDIENTS: ZINC OXIDE 77.5 mg/1 mL; TITANIUM DIOXIDE 58.7 mg/1 mL
INACTIVE INGREDIENTS: WATER; CAPRYLYL TRISILOXANE; ISODODECANE; ALCOHOL; MEDIUM-CHAIN TRIGLYCERIDES; SEA SALT; ALUMINUM OXIDE; PHENOXYETHANOL; MICA; EDETATE DISODIUM; POLYETHYLENE GLYCOL 500; GLYCERIN; ISOSTEARIC ACID; FERRIC OXIDE RED; ADENOSINE; ASCORBYL TETRAISOPALMITATE; NIACINAMIDE; TOCOPHEROL; DIAMOND; ALLANTOIN; XANTHAN GUM; GREEN TEA LEAF; PENTYLENE GLYCOL; TROMETHAMINE

RADICAL SKINCARE SKIN PERFECTING SCREEN SPF 30

Drug Facts

Active Ingredients:

Zinc Oxide 7.75%
Titanium Dioxide 5.87%

Purpose

Sunscreen

Uses

- helps prevent sunburn

Warnings

For external use only

Do not use

on damaged or broken skin

When using this product

keep out of eyes.
Rinse with water to remove.

Stop use and ask a doctor if

rash occurs

Keep out of reach of children.

If product is swallowed, get medical help or contact a Poison Control Center right away.

Directions

- apply liberally 15 minutes before sun exposure
- reapply:

- after 40 minutes of swimming or sweating
- immediately after towel drying
- at least every 2 hours

- Sun Protection Measures. Spending time in the sun increases your risk of skin cancer and early skin aging. To decrease this risk, regularly use a sunscreen wish a broad spectrum SPF of 15 or higher and other sun protection measures including:
- limit time in the sun, especially from 10 a.m. - 2 p.m.
- wear long-sleeved shirts, pants, hats and sunglasses
- children under 6 months: Ask a doctor

Inactive Ingredients

Water, Caprylyl Methicone, PEG-10 Dimethicone, Isododecane, Titanium Dioxide, Alcohol, Caprylic/Capric Triglyceride, Polymethylsilsesquioxane, Methyl Methacrylate Crosspolymer, Sea Salt, Alumina, Methicone, Polyhydroxystearic Acid, Phenoxyethanol, Mica, Disodium EDTA, PEG-10, Glycerin, Isostearic Acid, Iron Oxides, Adenosine, Lecithin, Ascorbyl Tetraisopalmitate, Niacinamide, Tocopherol, Diamond Powder, Allantoin, Xanthum Gum, Camellia Sinensis Leaf Extract, Coffee Arabica (Coffee) Seed Extract, Pentylene Glycol, Superoxide Dismutase, Tromethamine

Other information

- protect this product from excessive heat and direct sun

Questions or comments?

Call toll free 1-800-519-1852

Principal Label

RADICAL skincare

SKIN PERFECTING
SCREEN
SPF 30

Non-Chemical Sunscreen
UV Broad Spectrum
High Protection

TRYLACEL™

40mL 1.35 FL. OZ.

For all skin types.

The perfect partner of any Radical regimen, this lightweight matte lotion offers non-chemical sunscreen with high sunburn protection, and light diffusing pigments to visibly reduce the appearance of wrinkles and imperctions, a hint of tint for the perfect healthy radiance.

Shake well before use.
Use over moisturizer, prior to sun exposure. Keep out of eyes. Stop use if irritation occurs or increases. If irritation persists, consult a health care practitioner.

RADICAL BEAUTY
20 rue Cambon
75001 PARIS - FRANCE
made in France
www.radicalskincare.com